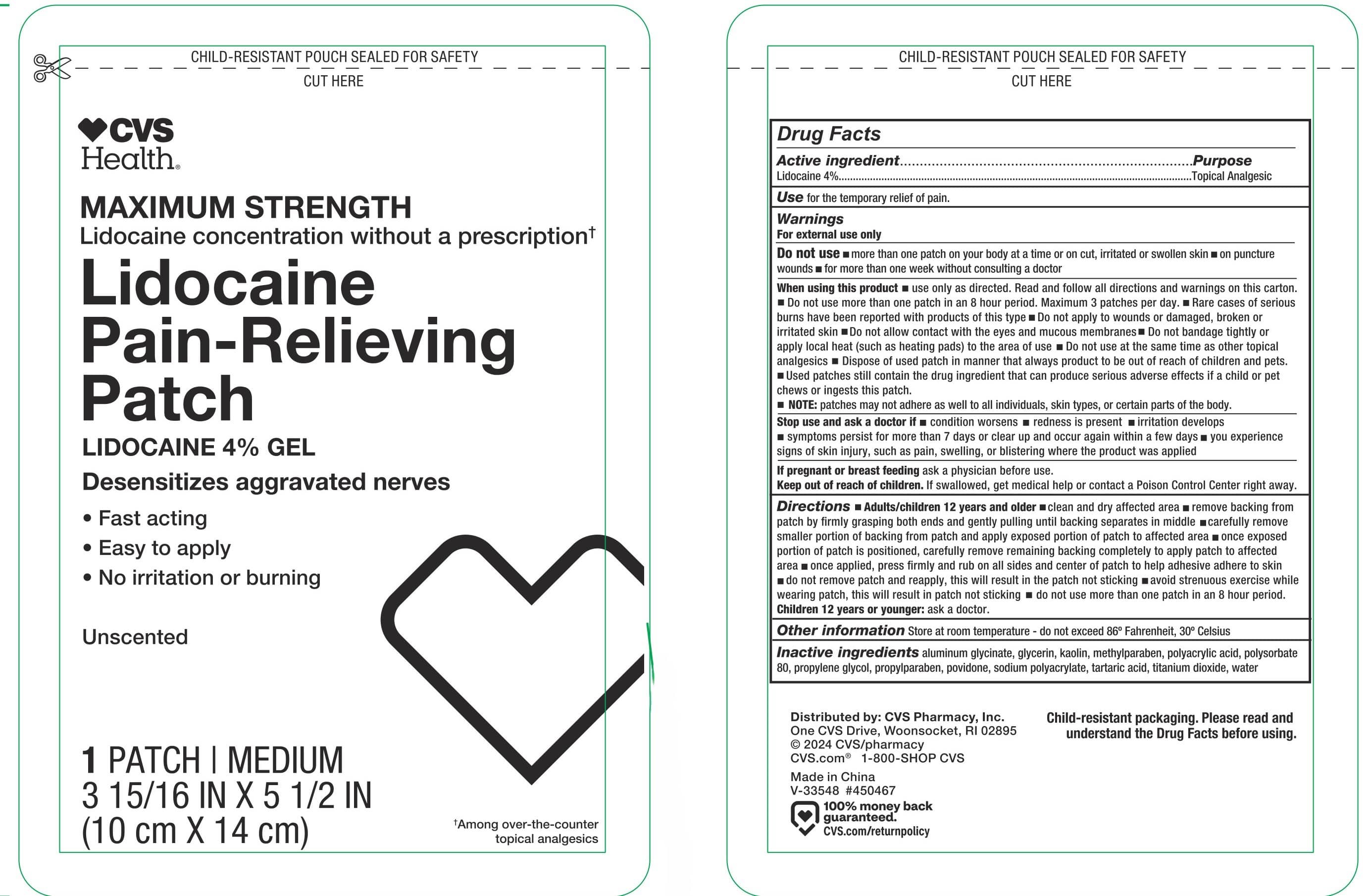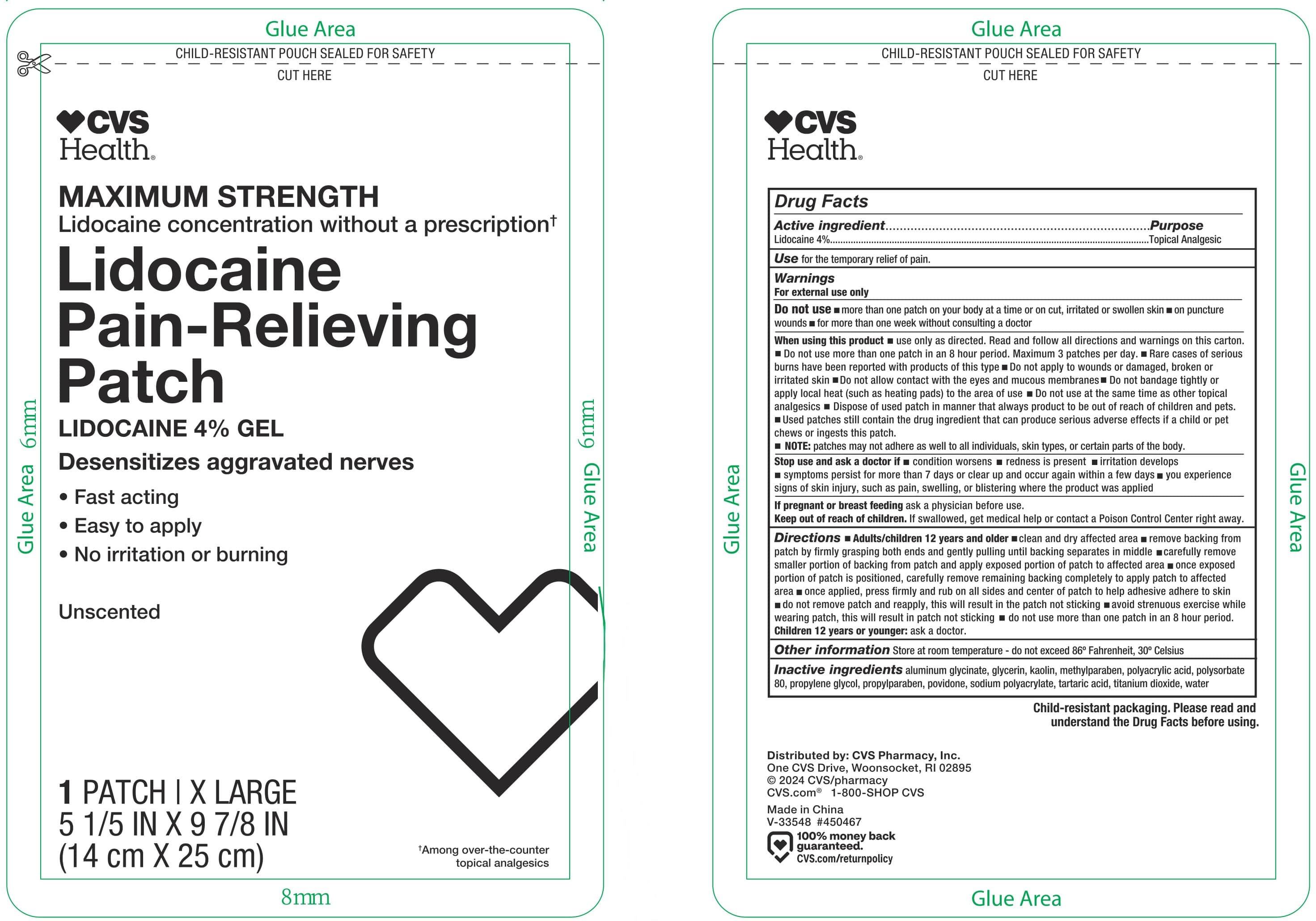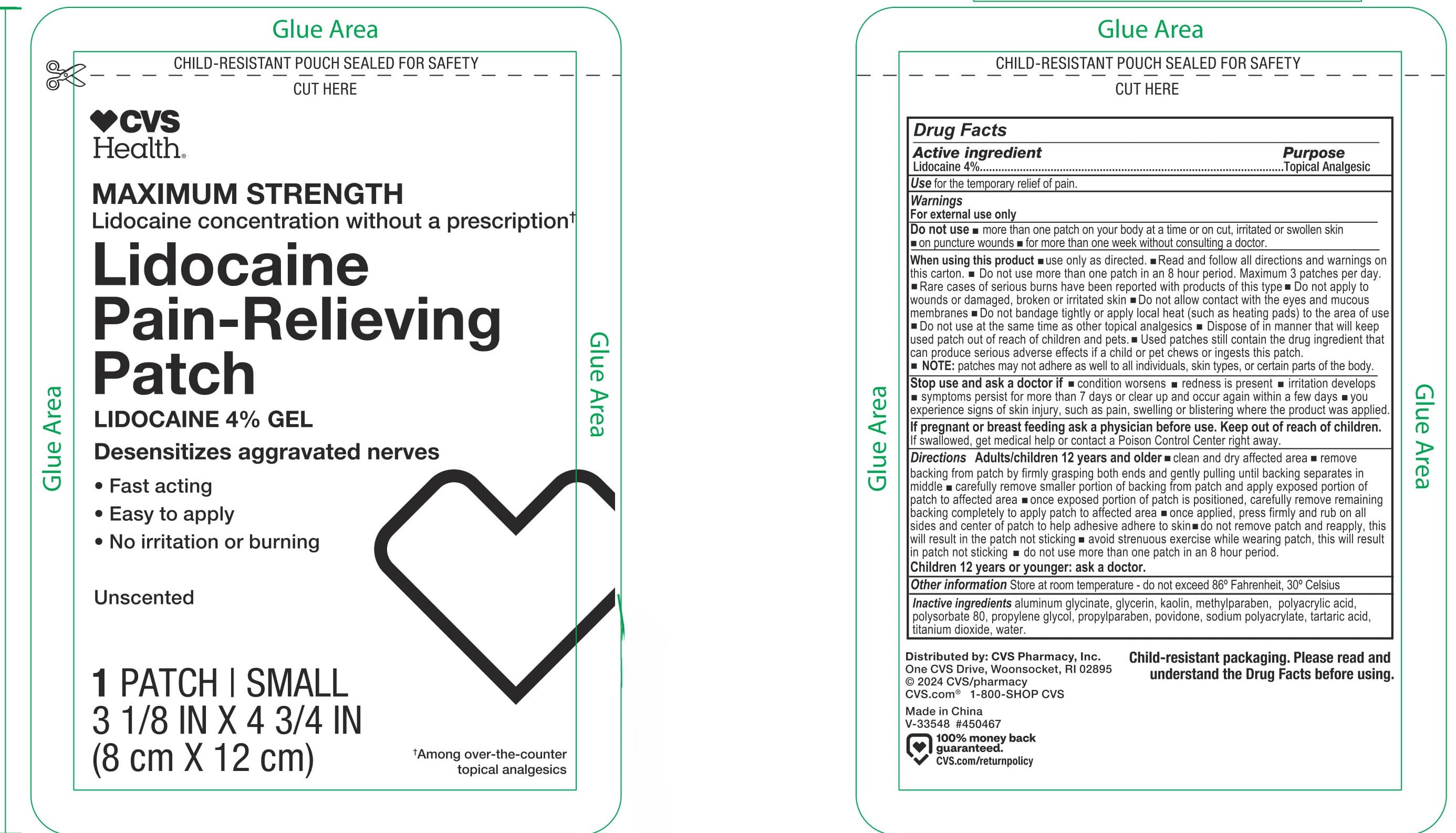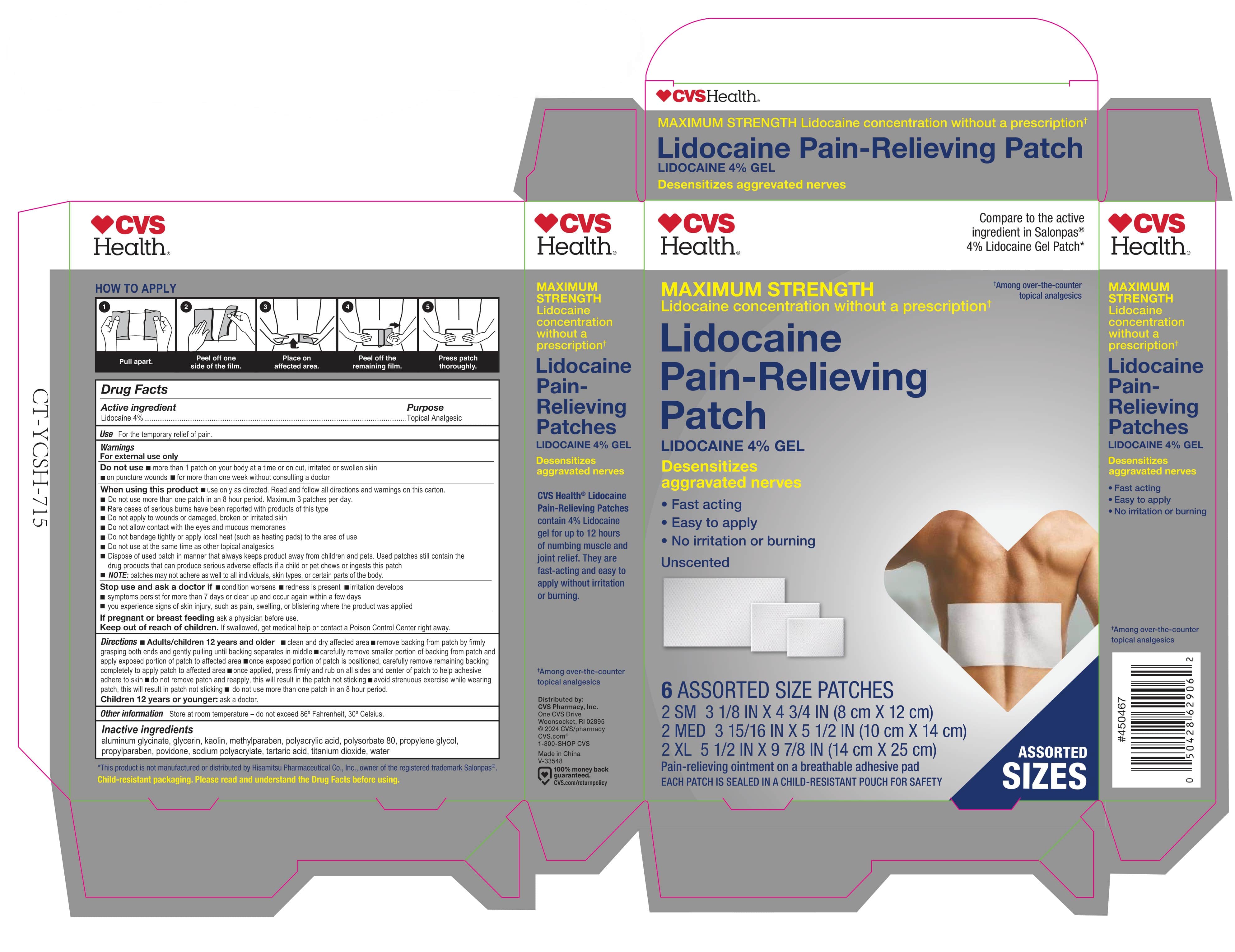 DRUG LABEL: CVS Health Lidocaine Pain-Relieving
NDC: 66902-450 | Form: KIT | Route: TRANSDERMAL
Manufacturer: NATURAL ESSENTIALS, INC.
Category: otc | Type: HUMAN OTC DRUG LABEL
Date: 20241014

ACTIVE INGREDIENTS: LIDOCAINE 40 mg/1 g; LIDOCAINE 40 mg/1 g; LIDOCAINE 40 mg/1 g
INACTIVE INGREDIENTS: DIHYDROXYALUMINUM AMINOACETATE ANHYDROUS; GLYCERIN; KAOLIN; METHYLPARABEN; POLYACRYLIC ACID (8000 MW); POLYSORBATE 80; PROPYLENE GLYCOL; PROPYLPARABEN; POVIDONE, UNSPECIFIED; SODIUM POLYACRYLATE (8000 MW); TARTARIC ACID; TITANIUM DIOXIDE; WATER; DIHYDROXYALUMINUM AMINOACETATE ANHYDROUS; GLYCERIN; KAOLIN; METHYLPARABEN; POLYACRYLIC ACID (8000 MW); POLYSORBATE 80; PROPYLENE GLYCOL; PROPYLPARABEN; POVIDONE, UNSPECIFIED; SODIUM POLYACRYLATE (8000 MW); TARTARIC ACID; TITANIUM DIOXIDE; WATER; DIHYDROXYALUMINUM AMINOACETATE ANHYDROUS; GLYCERIN; KAOLIN; METHYLPARABEN; POLYACRYLIC ACID (8000 MW); POLYSORBATE 80; PROPYLENE GLYCOL; PROPYLPARABEN; POVIDONE, UNSPECIFIED; SODIUM POLYACRYLATE (8000 MW); TARTARIC ACID; TITANIUM DIOXIDE; WATER

Drug Facts

Active ingredient

Lidocaine 4%

Purpose

Topical Analgesic

Use

For the temporary relief of pain.

Warnings

For external use only

Do not use

- more than 1 patch on your body at a time or on cut, irritated or swollen skin
- on puncture wounds
- for more than one week without consulting a doctor

When using this product

- use only as directed. Read and follow all directions and warnings on this carton.
- Do not use more than one patch in an 8 hour period. Maximum 3 patches per day.
- Rare cases of serious burns have been reported with products of this type
- Do not apply to wounds or damaged, broken or irritated skin
- Do not allow contact with the eyes and mucous membranes
- Do not bandage tightly or apply local heat (such as heating pads) to the area of use
- Do not use at the same time as other topical analgesics
- Dispose of used patch in manner that always keeps product away from children and pets. Used patches still contain the drug products that can produce serious adverse effects if a child or pet chews or ingests this patch
- NOTE:patches may not adhere as well to all individuals, skin types, or certain parts of the body.

Stop use and ask a doctor if

- condition worsens
- redness is present
- irritation develops
- symptoms persist for more than 7 days or clear up and occur again within a few days
- you experience signs of skin injury, such as pain, swelling, or blistering where the product was applied

PREGNANCY OR BREAST FEEDING

If pregnant or breast feedingask a physician before use.

Keep out of reach of children.If swallowed, get medical help or contact a Poison Control Center right away.

Directions

- Adults/children 12 years and older
- clean and dry affected area
- remove backing from patch by firmly grasping both ends and gently pulling until backing separates in middle
- carefully remove smaller portion of backing from patch and apply exposed portion of patch to affected area
- once exposed portion of patch is positioned, carefully remove remaining backing completely to apply patch to affected area
- once applied, press firmly and rub on all sides and center of patch to help adhesive adhere to skin
- do not remove patch and reapply, this will result in the patch not sticking a avoid strenuous exercise while wearing patch, this will result in patch not sticking
- do not use more than one patch in an 8 hour period.

Children 12 years or younger:ask a doctor.

Other information

Store at room temperature - do not exceed 86° Fahrenheit, 30° Celsius.

Inactive ingredients

aluminum glycinate, glycerin, kaolin, methylparaben, polyacrylic acid, polysorbate 80, propylene glycol, propylparaben, povidone, sodium polyacrylate, tartaric acid, titanium dioxide, water

Principal Display Panel – Carton Label

CVS
Health®

Compare to the active
ingredients in Salonpas®
4% Lidocaine Gel Patch*

MAXIMUM STRENGTH

Lidocaine concentration
without a prescription †

Lidocaine
Pain-Relieving
Patches

LIDOCAINE 4% GEL

Desensitizes
aggravated nerves

- Fast acting
- Easy to apply
- No irritation or burning

Unscented

6ASSORTED SIZE PATCHES

2 SM 3 1/8” x 4 ¾” (8 cm x 12 cm)

2 MED 3 15/16” x 5 1/2” (10 cm x 14 cm)

2 XL 5 1/2” x 9 7/8” (14 cm x 25 cm)

Pain-relieving ointment on a breathable adhesive pad

EACH PATCH IS SEALED IN A CHILD-RESISTANT POUCH FOR SAFETY

ASSORTED
SIZES

Principal Display Panel – Small Patch Label

CUT OPEN POUCH AND REMOVE PATCH

CVS
Health®

Compare to the active ingredient in
Salonpas®4% Lidocaine Gel Patch*

MAXIMUM STRENGTH

Lidocaine concentration without a prescription†

Lidocaine
Pain-Relieving
Patch

LIDOCAINE 4% GEL

Desensitizes aggravated nerves

- Fast acting
- Easy to apply
- No irritation or burning

Unscented

† Among over the counter
topical analgesics.

1PATCH | SMALL

3 1/8” x 4 3/4” (8 cm x 12 cm)

Principal Display Panel – Medium Patch Label

CUT OPEN POUCH AND REMOVE PATCH

CVS
Health®

Compare to the active ingredient in
Salonpas®4% Lidocaine Gel Patch*

MAXIMUM STRENGTH

Lidocaine concentration without a prescription†

Lidocaine
Pain-Relieving
Patch

LIDOCAINE 4% GEL

Desensitizes aggravated nerves

- Fast acting
- Easy to apply
- No irritation or burning

Unscented

† Among over the counter
topical analgesics.

1PATCH | MEDIUM

3 15/16” x 5 1/2” (10 cm x 14 cm)

Principal Display Panel – X Large Patch Label

CUT OPEN POUCH AND REMOVE PATCH

CVS
Health®

Compare to the active ingredient in
Salonpas®4% Lidocaine Gel Patch*

MAXIMUM STRENGTH

Lidocaine concentration without a prescription†

Lidocaine
Pain-Relieving
Patch

LIDOCAINE 4% GEL

Desensitizes aggravated nerves

- Fast acting
- Easy to apply
- No irritation or burning

Unscented

† Among over the counter
topical analgesics.

1PATCH | X LARGE

5 1/2” x 9 7/8” (14 cm x 25 cm)